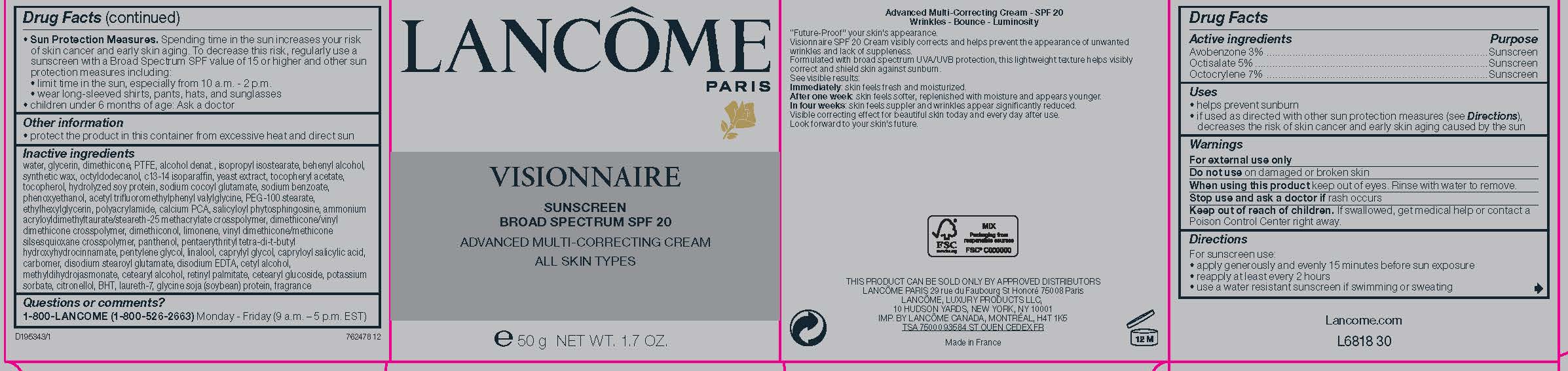 DRUG LABEL: Lancome Paris Visionnaire Broad Spectrum SPF 20 Sunscreen  Advanced Multi Correcting All Skin Types
NDC: 49967-194 | Form: CREAM
Manufacturer: L'Oreal USA Products Inc
Category: otc | Type: HUMAN OTC DRUG LABEL
Date: 20231230

ACTIVE INGREDIENTS: AVOBENZONE 30 mg/1 g; OCTISALATE 50 mg/1 g; OCTOCRYLENE 70 mg/1 g
INACTIVE INGREDIENTS: WATER; GLYCERIN; DIMETHICONE; POLYTETRAFLUOROETHYLENE; ALCOHOL; ISOPROPYL ISOSTEARATE; DOCOSANOL; SYNTHETIC WAX (1200 MW); OCTYLDODECANOL; C13-14 ISOPARAFFIN; YEAST, UNSPECIFIED; .ALPHA.-TOCOPHEROL ACETATE; TOCOPHEROL; HYDROLYZED SOY PROTEIN (ENZYMATIC; 2000 MW); SODIUM COCOYL GLUTAMATE; SODIUM BENZOATE; PHENOXYETHANOL; ACETYL TRIFLUOROMETHYLPHENYL VALYLGLYCINE, DL-; PEG-100 STEARATE; ETHYLHEXYLGLYCERIN; POLYACRYLAMIDE (10000 MW); CALCIUM PIDOLATE; SALICYLOYL PHYTOSPHINGOSINE; DIMETHICONE/VINYL DIMETHICONE CROSSPOLYMER (HARD PARTICLE); DIMETHICONOL (100000 CST); LIMONENE, (+)-; VINYL DIMETHICONE/METHICONE SILSESQUIOXANE CROSSPOLYMER; PANTHENOL; PENTAERYTHRITOL TETRAKIS(3-(3,5-DI-TERT-BUTYL-4-HYDROXYPHENYL)PROPIONATE); PENTYLENE GLYCOL; LINALOOL, (+/-)-; CAPRYLYL GLYCOL; CAPRYLOYL SALICYLIC ACID; CARBOMER HOMOPOLYMER TYPE B (ALLYL SUCROSE CROSSLINKED); EDETATE DISODIUM; CETYL ALCOHOL; METHYL DIHYDROJASMONATE (SYNTHETIC); CETOSTEARYL ALCOHOL; VITAMIN A PALMITATE; CETEARYL GLUCOSIDE; POTASSIUM SORBATE; .BETA.-CITRONELLOL, (R)-; BUTYLATED HYDROXYTOLUENE; LAURETH-7

Drug Facts

Active ingredients

Avobenzone 3%

Octisalate 5%

Octocrylene 7%

Purpose

Sunscreen

Uses

- helps prevent sunburn

- if used as directed with other sun protection measures (see Directions), decreases the risk of skin cancer and early skin aging caused by the sun

Warnings

For external use only

Do not use

on damaged or broken skin

When using this product

keep out of eyes. Rinse with water to remove.

Stop use and ask a doctor if

rash occurs

Keep out of reach of children.

If swallowed, get medical help or contact a Poison Control Center right away.

Directions

For sunscreen use:

● apply generously and evenly 15 minutes before sun exposure

● reapply at least every 2 hours

● use a water resistant sunscreen if swimming or sweating

● Sun Protection Measures. Spending time in the sun increases your risk of skin cancer and early skin aging. To decrease this risk, regularly use a sunscreen with a Broad Spectrum SPF value of 15 or higher and other sun protection measures including:

● limit time in the sun, especially from 10 a.m. – 2 p.m.

● wear long-sleeved shirts, pants, hats, and sunglasses

● children under 6 months of age: Ask a doctor

Other information

protect the product in this container from excessive heat and direct sun

Inactive ingredients

water, glycerin, dimethicone, PTFE, alcohol denat., isopropyl isostearate, behenyl alcohol, synthetic wax, octyldodecanol, C13-14 isoparaffin, yeast extract, tocopheryl acetate, tocopherol, hydrolyzed soy protein, sodium cocoyl glutamate, sodium benzoate, phenoxyethanol, acetyl trifluoromethylphenyl valylglycine, PEG-100 stearate, ethylhexylglycerin, polyacrylamide, calcium PCA, salicyloyl phytosphingosine, ammonium acryloyldimethyltaurate/steareth-25 methacrylate crosspolymer, dimethicone/vinyl dimethicone crosspolymer, dimethiconol, limonene, vinyl dimethicone/methicone silsesquioxane crosspolymer, panthenol, pentaerythrityl tetra-di-t-butyl hydroxyhydrocinnamate, pentylene glycol, linalool, caprylyl glycol, capryloyl salicylic acid, carbomer, disodium stearoyl glutamate, disodium EDTA, cetyl alcohol, methyldihydrojasmonate, cetearyl alcohol, retinyl palmitate, cetearyl glucoside, potassium sorbate, citronellol, BHT, laureth-7, glycine soja (soybean) protein

Questions or comments?

1-800-LANCOME (1-800-526-2663) Monday - Friday (9 a.m. - 5 p.m. EST)